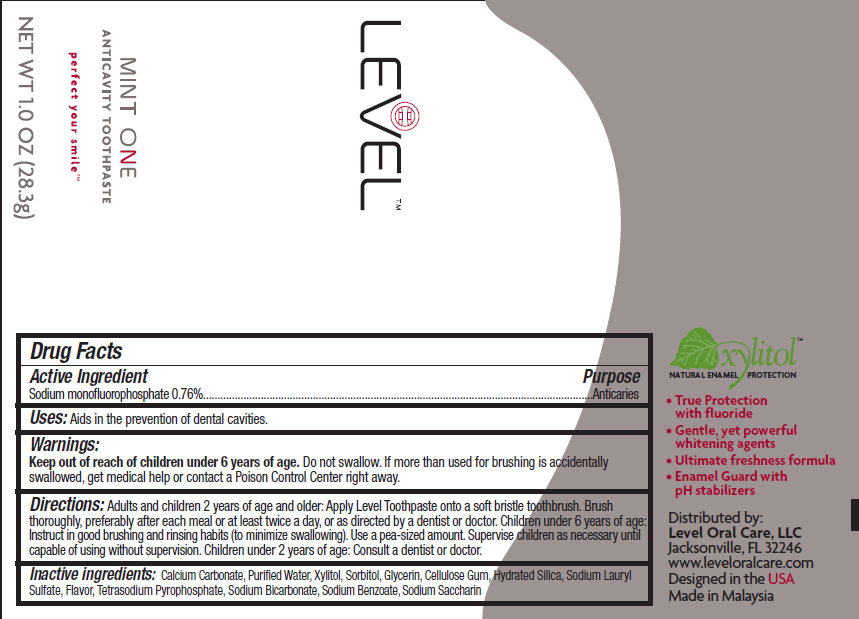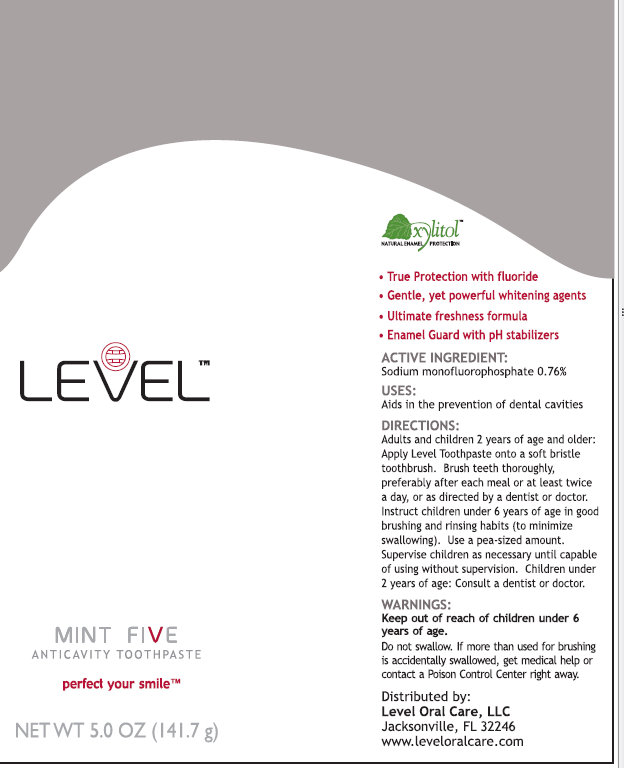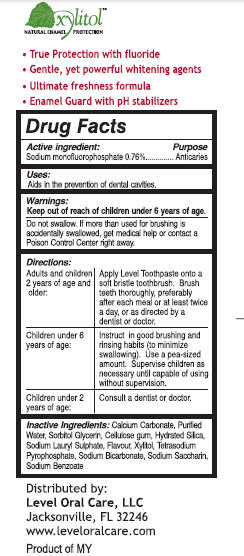 DRUG LABEL: Level Anticavity
NDC: 50001-111 | Form: PASTE
Manufacturer: Level Oral Care, LLC 
Category: otc | Type: HUMAN OTC DRUG LABEL
Date: 20110511

ACTIVE INGREDIENTS: SODIUM MONOFLUOROPHOSPHATE 76 g/100 g
INACTIVE INGREDIENTS: WATER; GLYCERIN; SORBITOL; XYLITOL; SILICON DIOXIDE; CALCIUM CARBONATE; SODIUM PYROPHOSPHATE; SODIUM LAURYL SULFATE; SODIUM BICARBONATE; SACCHARIN; CROSCARMELLOSE SODIUM; SODIUM BENZOATE

Level Mint Anticavity Toothpaste

Active Ingredient: Purpose

Sodium monofluorophoshate 0.76 percent Anticaries

Purpose
Anticaries

Uses:

Aids in the prevention of dental cavities.

Warnings:

Do not swallow. If more than used for brushing is accidentally swallowed, get medical help or contact a Poison Control Center right away.

KEEP OUT OF REACH OF CHILDREN

Keep out of reach children under 6 years of age.

Directions:

Adults and children 2 years of age and older: Apply Level Toothpaste onto a soft bristle toothbrush. Brush teeth thoroughly, preferably after each meal or at least twice a day, or as directed by a dentist or doctor.

Children under 6 years of age: Instruct in good brushing and rinsing habits (to minimize swallowing). Use a pea-sized amount. Supervise children as necessary until capable of using without supervision.

Children under 2 years of age: Consult a dentist or doctor.

INACTIVE INGREDIENT

Inactive Ingredients: purified water, glycerin, sorbitol, xylitol hydrated silica, calcium carbonate,

tetrasodium pyrophosphate, sodium lauryl sulfate, sodium bicarbonate, sodium saccharin,

cellulose gum, sodium benzoate, flavor

DESCRIPTION

xylitol

Natural Enamel Protection

True Protection with fluoride

Gentle, yet powerful whitening agents

Ultimate freshness formula

Enamel Guard with pH stabilizers

Distributed by:
Level Oral Care, LLC
Jacksonville, FL 32246
www.leveloralcare.com
Product of MY

PACKAGE LABEL

Level

Mint Five

Anticavity Toothpaste

perfect your smile

NET WT 5.0 oz (141.7 g)

DOSAGE FORMS AND STRENGTHS

Level
Mint One
Anticavity Toothpaste
perfect your smile
NET WT 1.0 oz (28.3 g)